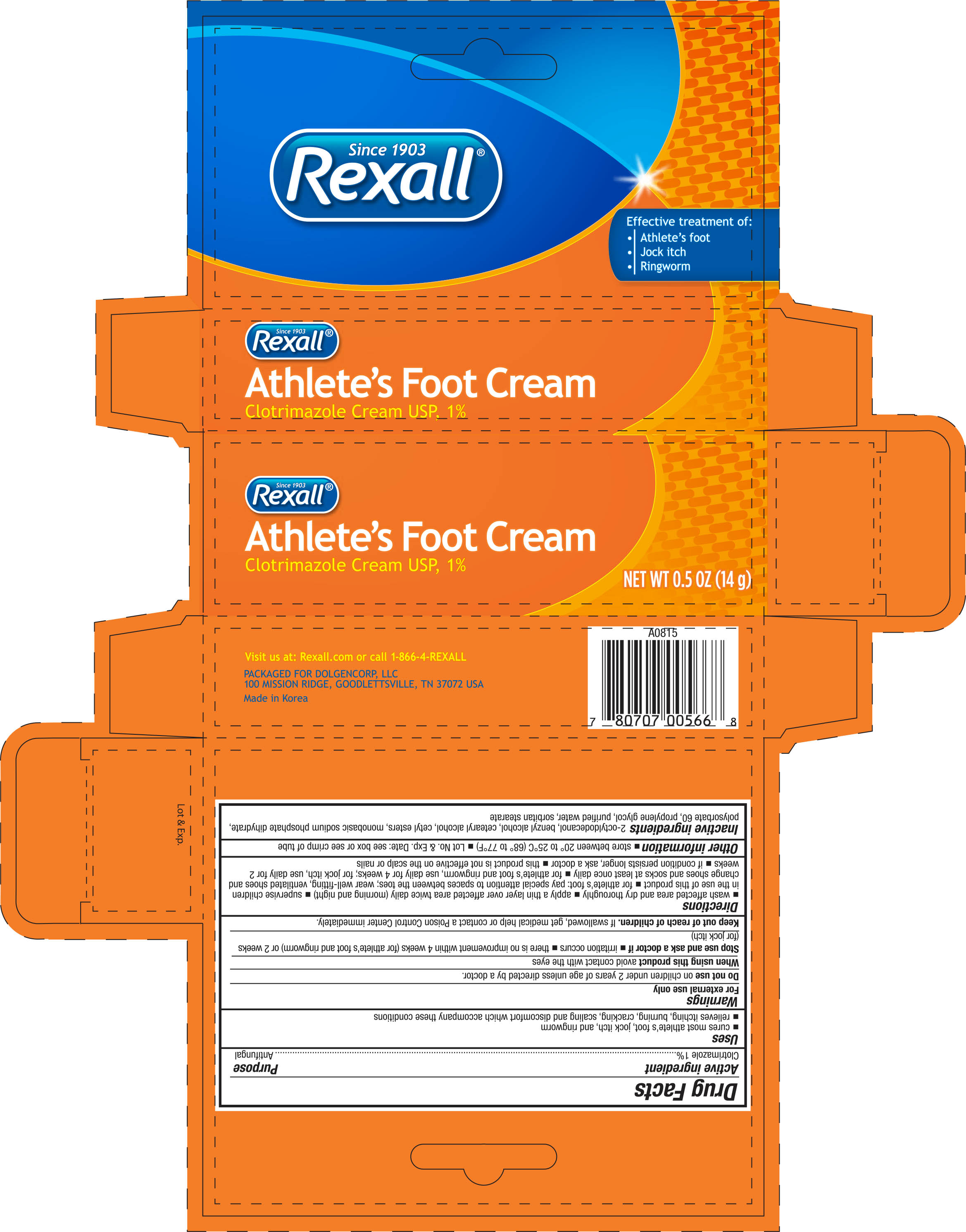 DRUG LABEL: Rexall Athletes Foot
NDC: 55910-566 | Form: CREAM
Manufacturer: Dolgencorp LLC
Category: otc | Type: HUMAN OTC DRUG LABEL
Date: 20181221

ACTIVE INGREDIENTS: CLOTRIMAZOLE 1 g/100 g
INACTIVE INGREDIENTS: OCTYLDODECANOL; BENZYL ALCOHOL; CETOSTEARYL ALCOHOL; CETYL ESTERS WAX; SODIUM PHOSPHATE, MONOBASIC, DIHYDRATE; POLYSORBATE 60; PROPYLENE GLYCOL; WATER; SORBITAN MONOSTEARATE

Rexall Athlete's Foot Cream 0.5 oz (566, 2018)

Active ingredient Purpose

Clotrimazole 1%................................................................. Antifungal

Uses

- cures most athlete's foot, jock itch, and ringworm
- relieves itching, burning, cracking, scaling, and discomfort which accompany these conditions

Warnings

For external use only

Do not use on children under 2 years of age unless directed by a doctor

When using this product avoid contact with the eyes

Stop use and ask a doctor if

- irritation occurs
- there is no improvement within 4 weeks (for athlete's foot and ringworm) or 2 weeks (for jock itch)

Keep out of reach of children. If swallowed, get medical help or contact a Poison Control Center immediately.

Directions

- wash affected area and dry thoroughly
- apply a thin layer over affected area twice daily (morning and night)
- supervise children in the use of this product
- for athlete's foot: pay special attention to spaces between the toes; wear well-fitting, ventilated shoes and change shoes and socks at least once daily
- for athlete's foot and ringworm, use daily for 4 weeks; for jock itch, use daily for 2 weeks
- if condition persists longer, ask a doctor
- this product is not effective on the scalp or nails

Other information

- store between 20° to 25°C (68° to 77°F)
- Lot No. & Exp. Date: see box or see crimp of tube

Inactive ingredients

2-octyldodecanol, benzyl alcohol, cetearyl alcohol, cetyl esters, monobasic sodium phosphate dihydrate, polysorbate 60, propylene glycol, purified water, sorbitan stearate

DOSAGE AND ADMINISTRATION

Distributed by:

Dolgencorp, LLC

100 Mission Ridge

Goodlettsville, TN 37072 USA

Made in Korea